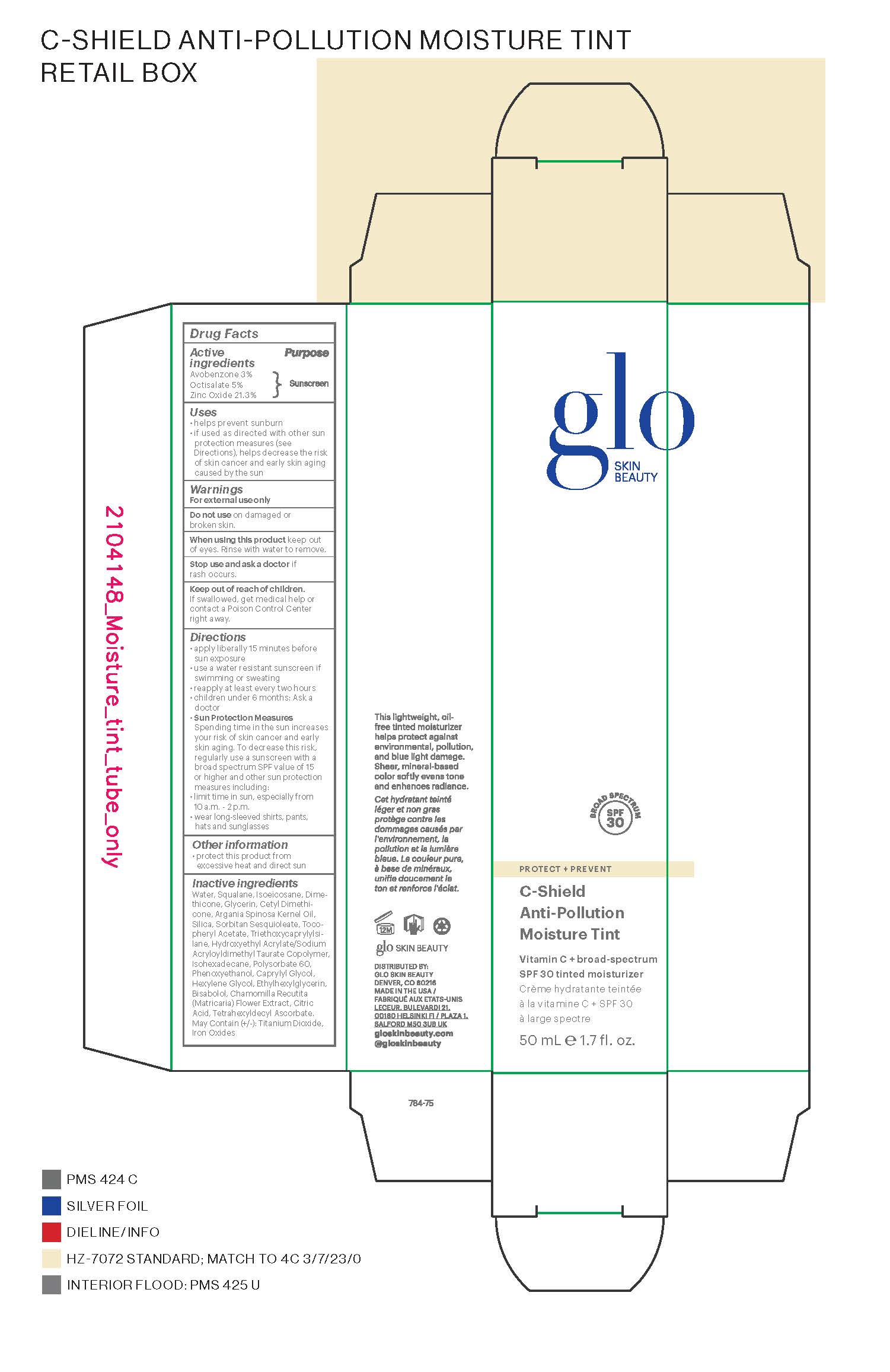 DRUG LABEL: glo Skin Beauty C-Shield Anti-Pollution Moisture Tint Broad Spectrum SPF 30
NDC: 60541-2000 | Form: CREAM
Manufacturer: Hayden Caleel LLC
Category: otc | Type: HUMAN OTC DRUG LABEL
Date: 20250105

ACTIVE INGREDIENTS: AVOBENZONE 3 g/100 g; OCTISALATE 5 g/100 g; ZINC OXIDE 21.3 g/100 g
INACTIVE INGREDIENTS: WATER; SQUALANE; ISOEICOSANE; DIMETHICONE; GLYCERIN; CETYL DIMETHICONE 25; ARGANIA SPINOSA LEAF; SILICON DIOXIDE; SORBITAN SESQUIOLEATE; .ALPHA.-TOCOPHEROL ACETATE; TRIETHOXYCAPRYLYLSILANE; HYDROXYETHYL ACRYLATE/SODIUM ACRYLOYLDIMETHYL TAURATE COPOLYMER (100000 MPA.S AT 1.5%); ISOHEXADECANE; POLYSORBATE 60; PHENOXYETHANOL; CAPRYLYL GLYCOL; HEXYLENE GLYCOL; ETHYLHEXYLGLYCERIN; BISABOLOL OXIDE A; MATRICARIA CHAMOMILLA; CITRIC ACID MONOHYDRATE; TETRAHEXYLDECYL ASCORBATE

DRUG FACTS

Active Ingredients

Avobenzone 3%

Octisalate 5%

Zinc Oxide 4%

Uses

• helps prevent sunburn • if used as directed with other
sun protection measures (see Directions), decreases the
risk of skin cancer and early skin aging caused by the sun

Warnings

For external use only
Do not use on damaged or broken skin
When using this product keep out of eyes. Rinse with water to remove.
Stop use and ask a docor if rash occurs
Keep out of reach of children. If swalled, get medical help or contact a Poison Control Center right away.

Directions

• apply liberally 15 minutes before sun exposure
• use a water-resistant sunscreen if swimming or sweating
• reapply at least every two hours•Sun Protection Measures. Spending time in the sunincreases your risk of skin cancer and early skin aging. To decreasethis risk, regularly use a sunscreen with a Broad Spectrum SPFvalue of 15 or higher and other sun protection measures including:

• limit time in the sun, especially from 10 a.m. - 2 p.m.
• wear long-sleeved shirts, pants, hats, and sunglasses
• children under 6 months of age: Ask a doctor

Inactive ingredients

Water, Squalane, Isoeicosane, Dimethicone,
Glycerin, Cetyl Dimethicone,
Argania Spinosa Kernel Oil,
Silica, Sorbitan Sesquioleate, Tocopheryl
Acetate, Triethoxycaprylylsilane,
Hydroxyethyl Acrylate/Sodium
Acryloyldimethyl Taurate Copolymer,
Isohexadecane, Polysorbate 60,
Phenoxyethanol, Caprylyl Glycol,
Hexylene Glycol, Ethylhexylglycerin,
Bisabolol, Chamomilla Recutita
(Matricaria) Flower Extract, Citric
Acid, Tetrahexyldecyl Ascorbate.
May Contain (+/-): Titanium Dioxide,
Iron Oxides

Other Information

• protect the product in this container from excessive
heat and direct sun

Keep out of reach of children

Purpose

Sunscreen